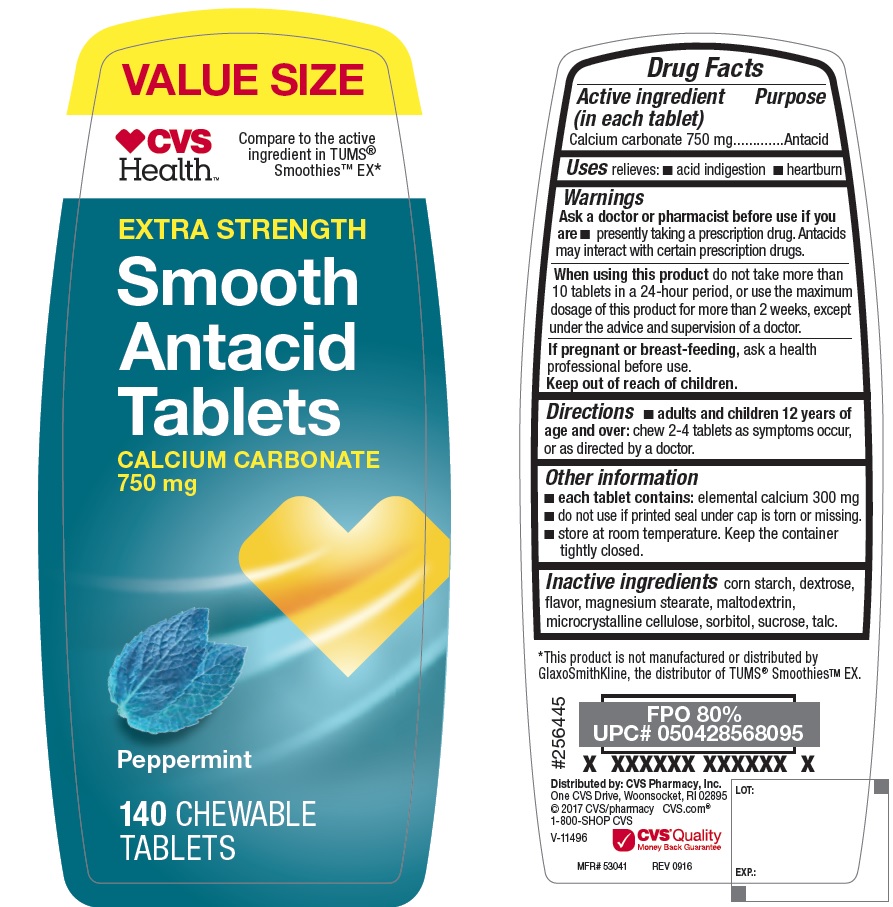 DRUG LABEL: Extra Strength Smooth Antacid
NDC: 69842-716 | Form: TABLET, CHEWABLE
Manufacturer: CVS
Category: otc | Type: HUMAN OTC DRUG LABEL
Date: 20170508

ACTIVE INGREDIENTS: CALCIUM CARBONATE 750 mg/1 1
INACTIVE INGREDIENTS: DEXTROSE; MAGNESIUM STEARATE; STARCH, CORN; SORBITOL; SUCROSE; TALC; MALTODEXTRIN; CELLULOSE, MICROCRYSTALLINE

Extra Strength Smooth Antacid Peppermint Tablets

Active ingredient (in each tablet)

Calcium carbonate 750 mg

Purpose

Antacid

Uses

relieves: acid indigestion, heartburn

Warnings

Ask a doctor or pharmacist before use if you are

- presently taking a prescription drug. Antacids may interact with certain prescription drugs.

When using this product

do not take more than 10 tablets in a 24-hour period, or use the maximum dosage of this product for more than 2 weeks, except under the advice and supervision of a doctor.

If pregnant or breast-feeding ask a health professional before use.

Keep out of reach of children

Directions

- adults and children 12 years of age and over: chew 2-4 tablets as symptoms occur, or as directed by a doctor

Other information

- each tablet contains: elemental calcium 300 mg
- do not use if pull tab seal under cap is torn or missing
- store at room temperature. keep the container tightly closed.

Inactive ingredients

corn starch, dextrose, flavors, magnesium stearate, maltodextrin, microcrystalline cellulose, sorbitol, sucrose, talc

PDP

Compare to TUMS® Smoothies E-X active ingredient

Extra Strength Smooth Antacid Tablets

Calcium Carbonate 750 mg

Peppermint

140 chewable Tablets